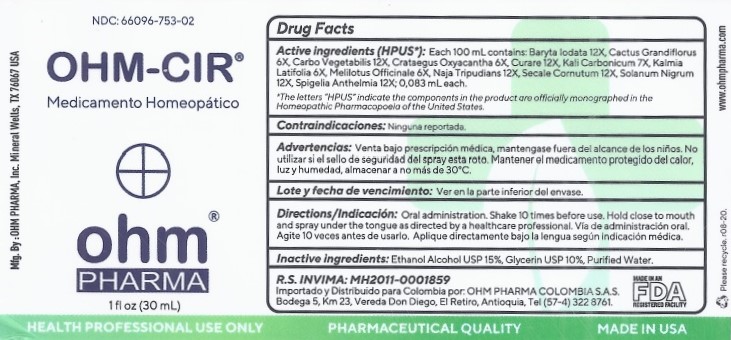 DRUG LABEL: OHM-CIR
NDC: 66096-753 | Form: SPRAY
Manufacturer: OHM PHARMA INC.
Category: homeopathic | Type: HUMAN PRESCRIPTION DRUG LABEL
Date: 20210325

ACTIVE INGREDIENTS: BARIUM IODIDE 12 [hp_X]/30 mL; SELENICEREUS GRANDIFLORUS STEM 6 [hp_X]/30 mL; ACTIVATED CHARCOAL 12 [hp_X]/30 mL; HAWTHORN LEAF WITH FLOWER 6 [hp_X]/30 mL; TUBOCURARINE CHLORIDE 12 [hp_X]/30 mL; POTASSIUM CARBONATE 7 [hp_X]/30 mL; KALMIA LATIFOLIA LEAF 6 [hp_X]/30 mL; MELILOTUS OFFICINALIS TOP 6 [hp_X]/30 mL; NAJA NAJA VENOM 12 [hp_X]/30 mL; CLAVICEPS PURPUREA SCLEROTIUM 12 [hp_X]/30 mL; SOLANUM NIGRUM TOP 12 [hp_X]/30 mL; SPIGELIA ANTHELMIA 12 [hp_X]/30 mL
INACTIVE INGREDIENTS: ALCOHOL; GLYCERIN; WATER

OHM-CIR

ACTIVE INGREDIENT

Active ingredients (HPUS*): 100 ml contains: Baryta Iodata 12X, Cactus Grandiflorus 6X, Carbo Vegetabilis 12X, Crataegus Oxyacantha 6X, Curare 12X, Kali Carbonicum 7X, Kalmia Latifolia 6X, Melilotus Officinale 6X, Naja Tripudians 12X, Secale Cornutum 12X, Solanum Nigrum 12X, Spigelia Anthelmia 12X; 0.083 mL each.

*The letters "HPUS" indicate the components in the product are officially monographed in the Homeopathic Pharmacopoeia of the United States.

INDICATIONS AND USAGE

Contraindicaciones: Ninguna reportada

WARNINGS

Advertencias:Venta bajo prescripción médica, mantengase fuera del alcance de los niños. No utilizar si el sello de seguridad del spray esta roto. Mantener el medicamento protegido del calor, luz y humedad, almacenar a no más de 30°C.

KEEP OUT OF REACH OF CHILDREN

Mantengase fuera del alcance de los niños.

DOSAGE AND ADMINISTRATION

Directions / Indicacion: Oral administration. Shake 10 times before use. Hold close to mouth and spray under the tongue as directed by a healthcare professional. Via de administracion oral. Agite 10 veces antes de usarlo. Aplique directamente bajo la lengua segun indicacion medica.

OTHER SAFETY INFORMATION

Lote y fecha de vencimiento: Ver en la parte inferior del envase

INACTIVE INGREDIENT

Inactive ingredients: Ethanol Alcohol USP 15%, Glycerin USP 10%, Purified Water.

QUESTIONS

R.S. INVIMA: MH2010-0001591
Importado y Distribuido para Colombia por: OHM PHARMA COLOMBIA S.A.S.
Bodega 5, Km 23, Vereda Don Diego, El Retiro, Antioquia, Tel (57-4) 322 8761.

Mfg. By : OHM PHARMA, Inc.
Mineral Wells, TX 76067 USA
www.ohmpharma.com

PACKAGE LABEL

NDC: 66096-753-02

OHM-CIR

Medicamento Homeopatico